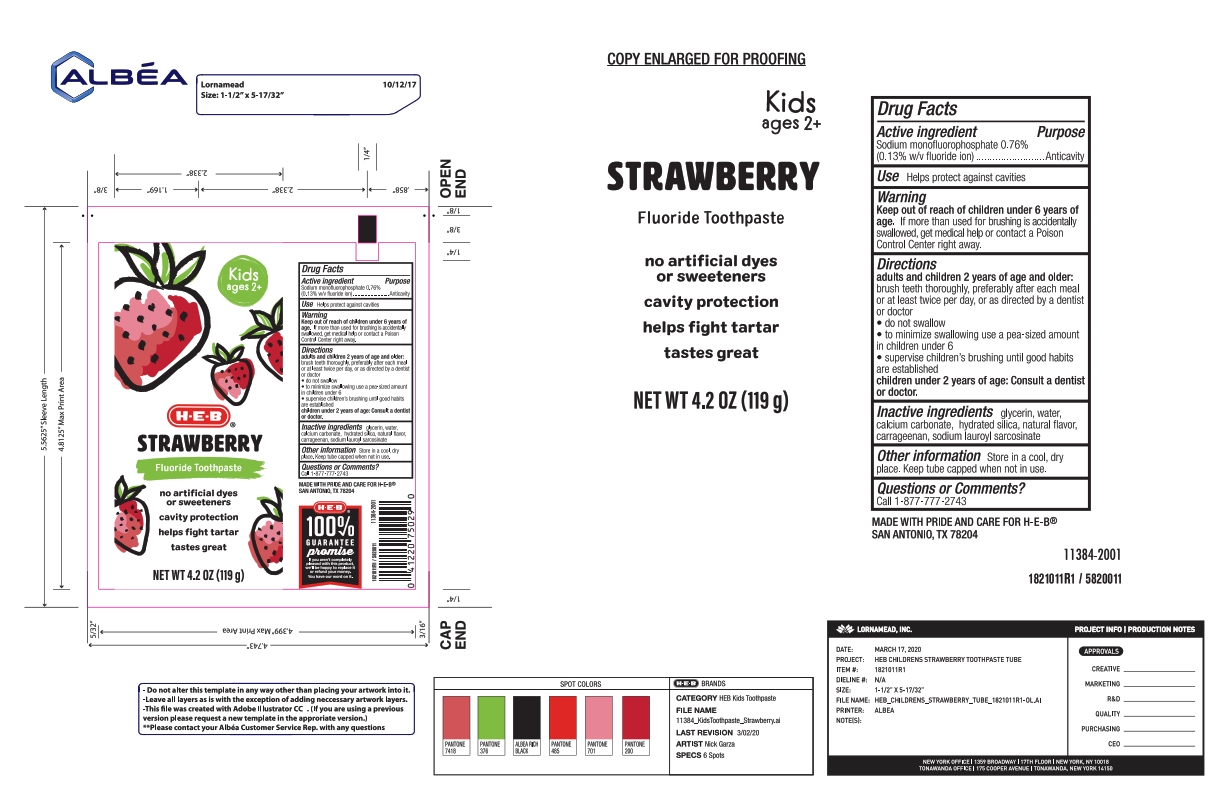 DRUG LABEL: Kids Silly Strawberry TP
NDC: 37808-411 | Form: PASTE, DENTIFRICE
Manufacturer: HEB
Category: otc | Type: HUMAN OTC DRUG LABEL
Date: 20251112

ACTIVE INGREDIENTS: SODIUM MONOFLUOROPHOSPHATE 0.13 g/100 g
INACTIVE INGREDIENTS: HYDRATED SILICA; CALCIUM CARBONATE; WATER; SODIUM LAUROYL SARCOSINATE; CARRAGEENAN; GLYCERIN

5820011 HEb Kid's Strawberry w/Fluroide TP (80-15276)

ACTIVE INGREDIENT

Sodium monofluorophosphate 0.76% (0.13% fluoride ion)

PURPOSE

Anticavity

INDICATIONS AND USAGE

Helps protect against cavities

WARNINGS

Keep out of reach of children under 6 years of age. If more than used for brushing is accidentally swallowed, get medical help or contact a Poison Control Center right away.

DOSAGE AND ADMINISTRATION

Adults and children 2 years of age and older: brush teeth thoroughly, preferably after each meal or at least twice a day, or as directed by a dentist or doctor

* do not swallow

* to minimize swallowing use a pea-sized amoutn in children under 6

* supervise children's brushing until good habits are established

Children under 2 years of age: consult a dentist or doctor.

INACTIVE INGREDIENT

glycerin, water, calcium carbonate, hydrated silica, natural flavor, carrageenan, sodium lauroyl sarcosinate

OTHER SAFETY INFORMATION

Store in a cool, dry place. Keep tube capped when not in use.